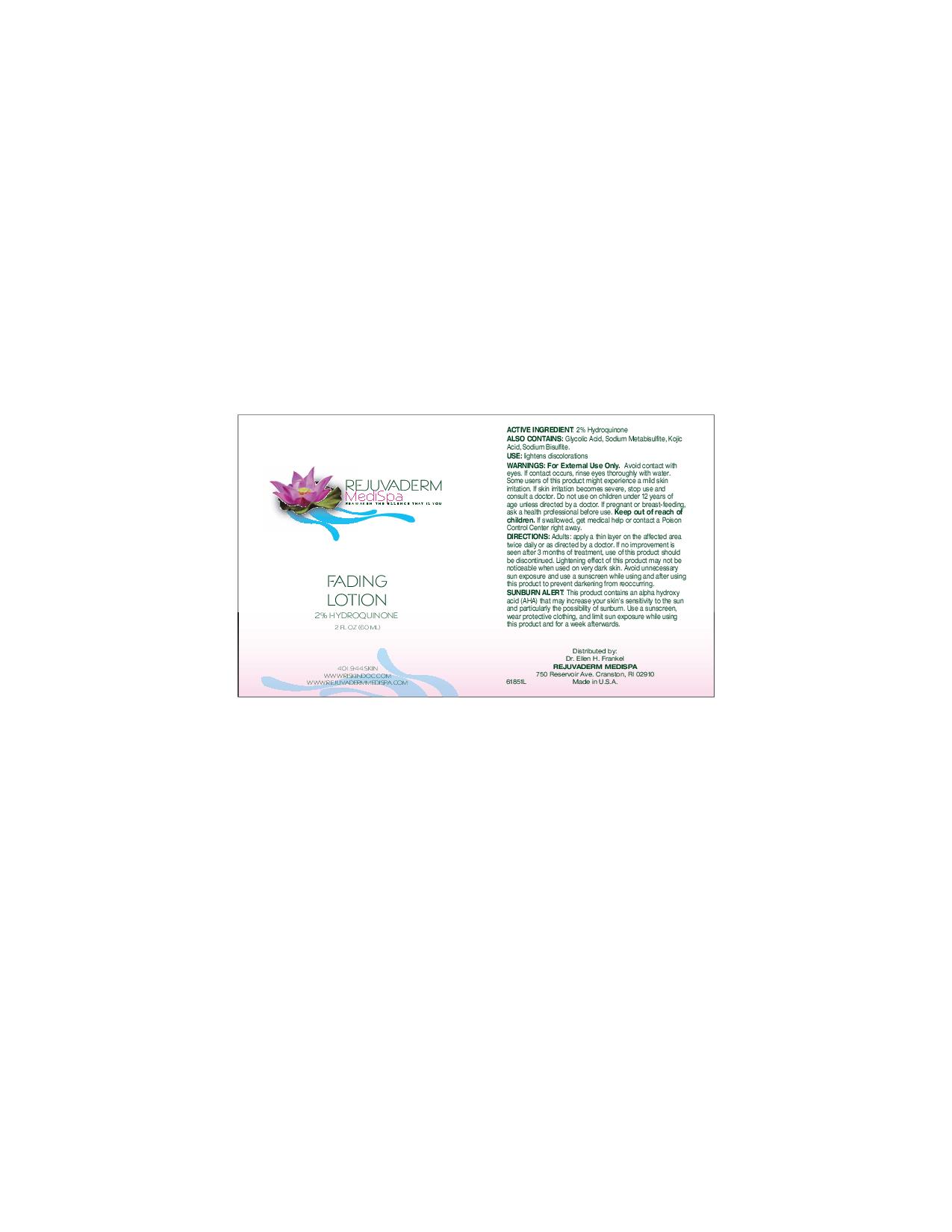 DRUG LABEL: Rejuvaderm medispa fading
NDC: 51325-300 | Form: LOTION
Manufacturer: Ellen H Frankle MD Inc
Category: otc | Type: HUMAN OTC DRUG LABEL
Date: 20100803

ACTIVE INGREDIENTS: hydroquinone 1.2 mL/60 mL

Rejuvaderm medispa Fading

Active Ingredient: 2% hydroquinone

INACTIVE INGREDIENT

Also contains: Glycolic acid, Sodium metabisulfite, Kojic acid, Sodium Bisulfite.

INDICATIONS AND USAGE

Use: lightens discolorations

DOSAGE AND ADMINISTRATION

Directions: adults: apply a thin layer on the affected area twice daily or as directed by a doctor. If no improvement is seen after 3 months of treatment, use of this product should be discontinued. Lightening effect of this product may nt be noticeable when used on very dark skin. Avoid unnecessary sun exposure and use a sunscreen while using and after using this product to prevent darkening from reoccurring.

WARNINGS

Warnings: For External Use Only. Avoid contact with eyes. If contact occurs, rinse eyes thoroughly with water. some users of this product might experience a mild skin irritation.If skin irritation becomes severe, stop use and consult a doctor. Do not use on children under 12 years of age unless directed by a doctor. If
pregnant or breast-feeding, ask a health professional before use. Keep out of reach of children. If swallowed, get medical help or contact a Poison Control Center right away.

GENERAL PRECAUTIONS

Sunburn Alert: This product contains an alpha hydroxy acid (AHA) that may increase your skin's sensitivity to the sun and particularly the possibility of sunburn. Use a sunscreen, wear protective clothing, and limit sun exposure while using this product and for a week afterwards.

Purpose: Skin Bleaching

Keep out of reach of children.

PACKAGE LABEL

Rejuvaderm Medispa

reawakens the essence that is you

Fading Lotion

2% hydroquinone

2 fl oz. (60 ml)

401944skin

wwwriskindoc.com

www.rejuvadermmedispa.com